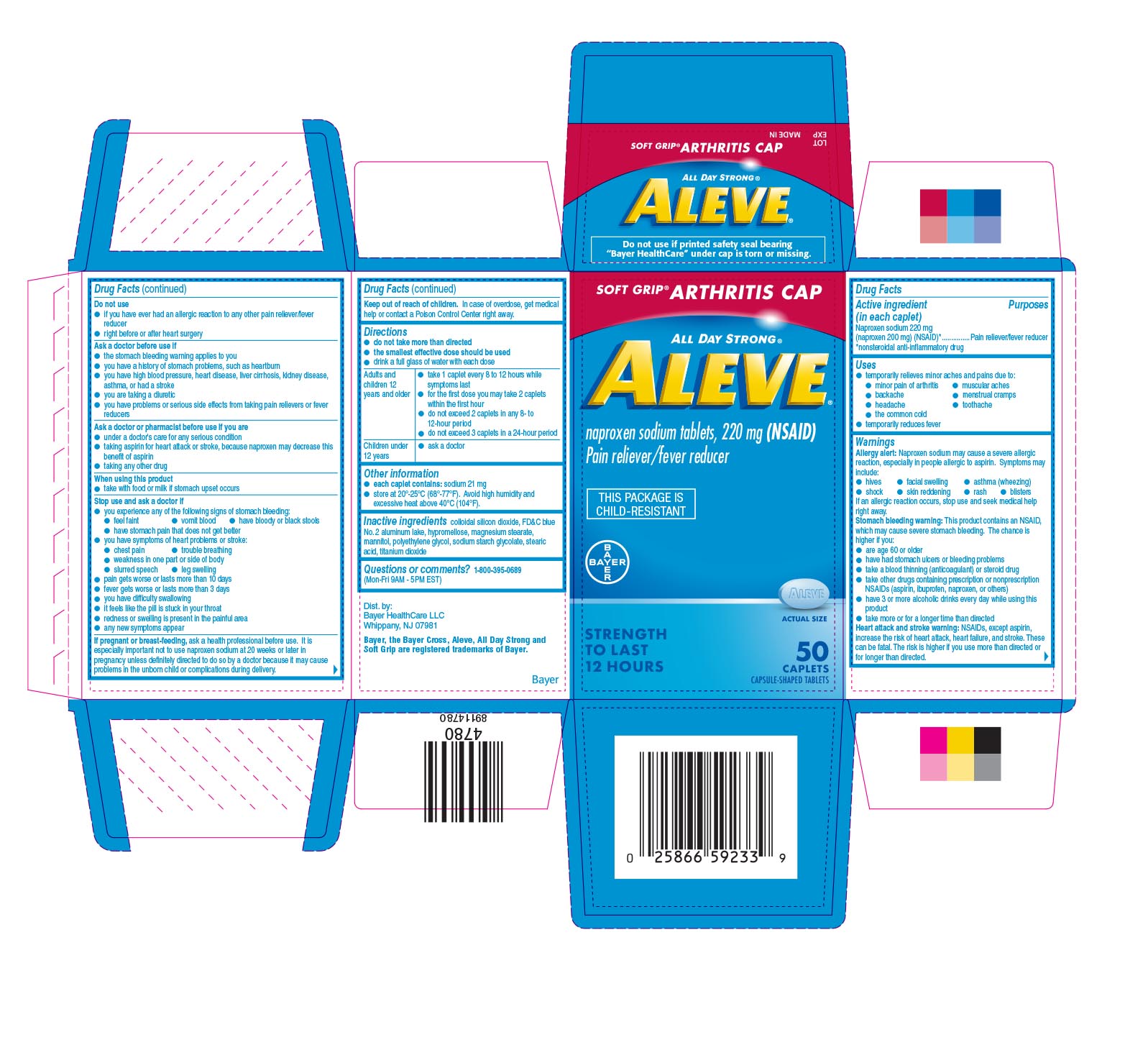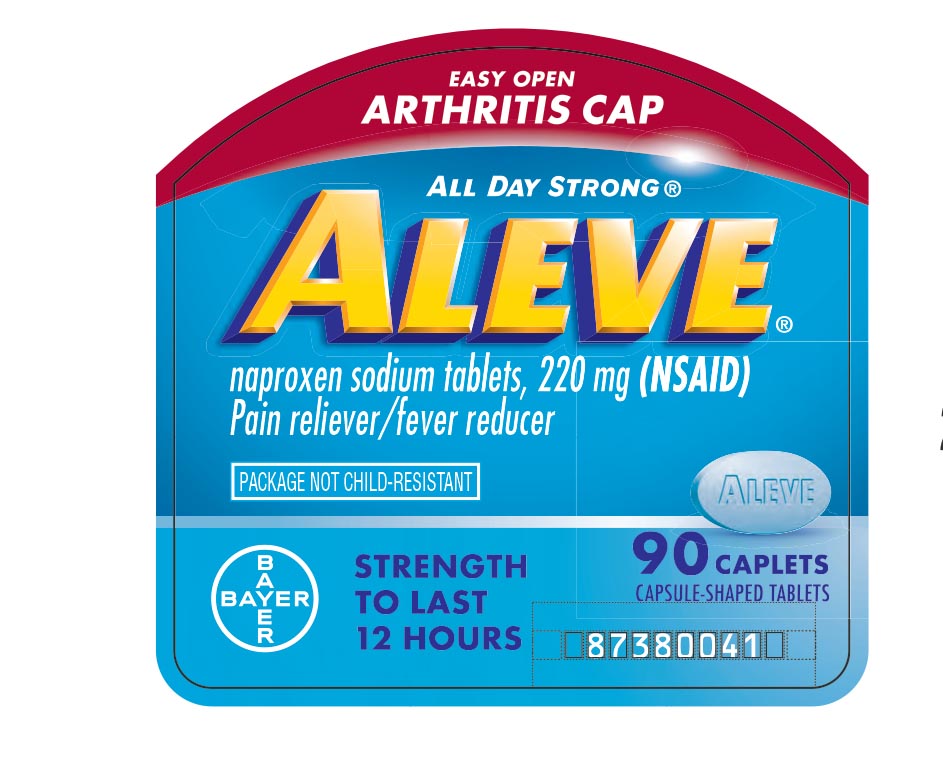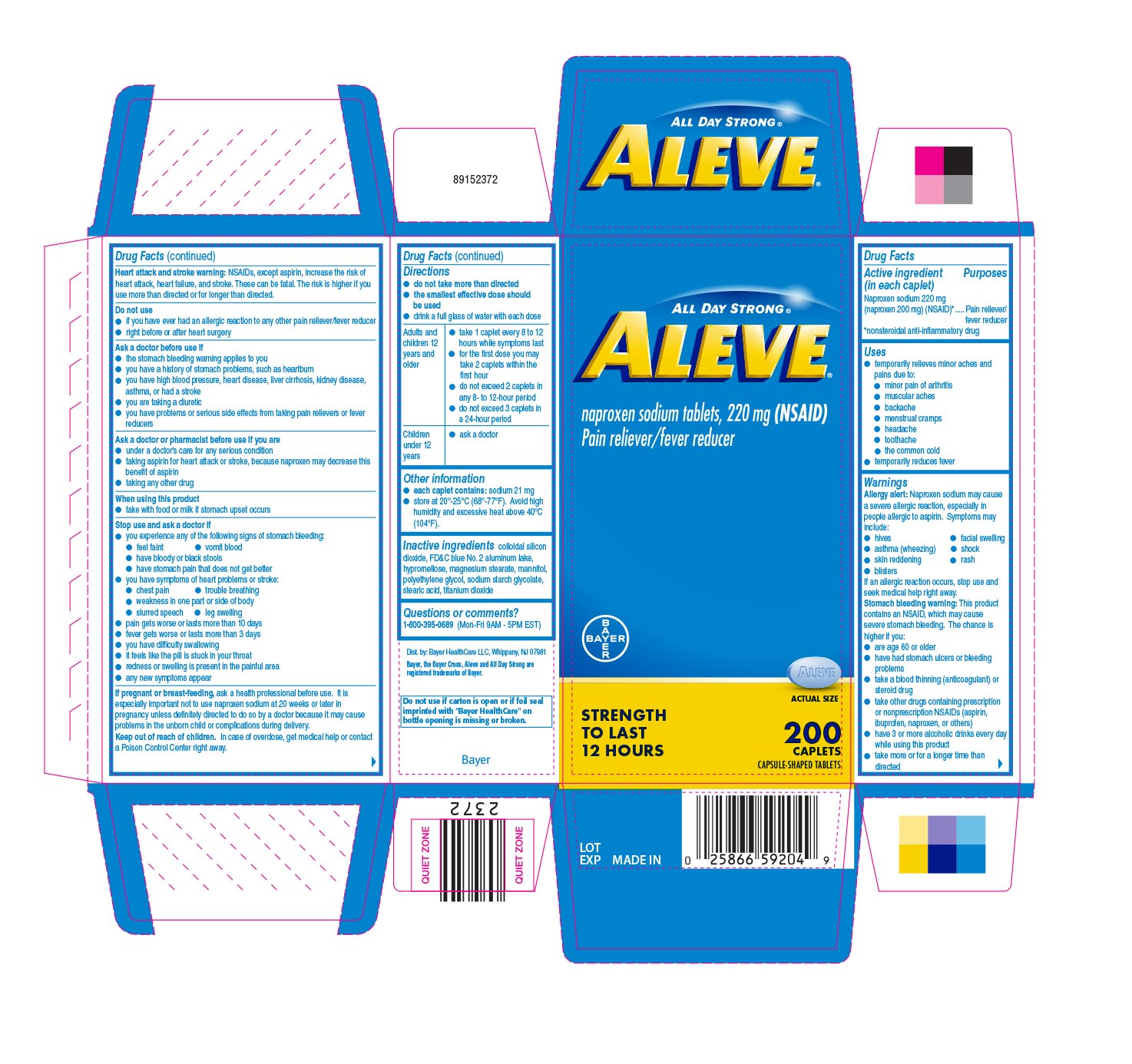 DRUG LABEL: Aleve
NDC: 85237-1832 | Form: TABLET
Manufacturer: Select Consumer Group
Category: otc | Type: HUMAN OTC DRUG LABEL
Date: 20251228

ACTIVE INGREDIENTS: NAPROXEN SODIUM 220 mg/1 1
INACTIVE INGREDIENTS: SILICON DIOXIDE; POLYETHYLENE GLYCOL, UNSPECIFIED; FD&C BLUE NO. 2; HYPROMELLOSES; MAGNESIUM STEARATE; MANNITOL; SODIUM CARBOXYMETHYL STARCH; TITANIUM DIOXIDE; STEARIC ACID

Aleve®Caplets - Blueshield UI 1614642

Drug Facts

Active ingredient (in each caplet)

Naproxen sodium 220 mg (naproxen 200 mg) (NSAID) [*nonsteroidal anti-inflammatory drug]

Purposes

Pain reliever/fever reducer

Uses

- temporarily relieves minor aches and pains due to:
  - minor pain of arthritis
  - muscular aches
  - backache
  - menstrual cramps
  - headache
  - toothache
  - the common cold

- temporarily reduces fever

Allergy alert: Naproxen sodium may cause a severe allergic reaction, especially in people allergic to aspirin. Symptoms may Include:

- hives
- facial swelling
- asthma (wheezing)
- shock
- skin reddening
- rash
- blisters

If an allergic reaction occurs, stop use and seek medical help right away

Stomach bleeding warning: This product contains an NSAID, which may cause severe stomach bleeding. The chance is higher if you:

- are age 60 or older
- have had stomach ulcers or bleeding problems
- take a blood thinning (anticoagulant) or steroid drug
- take other drugs containing prescription or nonprescription NSAIDs (aspirin, ibuprofen, naproxen, or others)
- have 3 or more alcoholic drinks every day while using this product
- take more or for a longer time than directed

Heart attack and stroke warning:NSAIDs, except aspirin, increase the risk of heart attack, heart failure, and stroke. These can be fatal. The risk is higher if you use more than directed or for longer than directed.

Do not use

- if you have ever had an allergic reaction to any other pain reliever/fever reducer
- right before or after heart surgery

Ask a doctor before use if

- the stomach bleeding warning applies to you
- you have a history of stomach problems, such as heartburn
- you have high blood pressure, heart disease, liver cirrhosis, kidney disease, asthma, or had a stroke
- you are taking a diuretic
- you have problems or serious side effects from taking pain relievers or fever reducers

Ask a doctor or pharmacist before use if you are

- under a doctor's care for any serious conidtion
- taking aspirin for heart attack or stroke, because naproxen may decrease this benefit of aspirin
- taking any other drug

When using this product

- take with food or milk if stomach upset occurs

Stop use and ask a doctor if

- you experience any of the following signs of stomach bleeding:
  - feel faint
  - vomit blood
  - have bloody or black stools
  - have stomach pain that does not get better

- you have symptoms of heart problems or stroke:
  - chest pain
  - trouble breathing
  - weakness in one part or side of body
  - slurred speech
  - leg swelling

- pain gets worse or lasts more than 10 days
- fever gets worse or lasts more than 3 days
- you have difficulty swallowing
- it feels like the pill is stuck in your throat
- redness or swelling is present in the painful area
- any new symptoms appear

PREGNANCY OR BREAST FEEDING

If pregnant or breast-feeding, ask a healthcare professional before use. It is especially important not to use naproxen sodium at 20 weeks or later in pregnancy unless definitely directed to do so by a doctor because it may cause problems un the unborn child or complications during delivery.

Keep out of reach of children.In case of overdose, get medical help or contact a Poison Control Center right away.

Directions

- do not take more than directed
- the smallest effective dose should be used
- drink a full glass of water with each dose

Adults and children 12 years and older | - take 1 caplet every 8 to 12 hours while symptoms last - for the first dose you may take 2 caplets within the first hour - do not exceed 2 caplets in any 8- to 12-hour period - do not exceed 3 caplets in a 24-hour period
Children under 12 years | - ask a doctor

Other information

- each caplet contains:sodium 21 mg
- store at 20-25 ° C (68-77 ° F). Avoid high humidity and excessive heat above 40 ° C (104 ° F).

Inactive ingredients

colloidal silicon dioxide, FD&C blue No. 2 aluminum lake, hypromellose, magnesium stearate, mannitol, polyethylene glycol, sodium starch glycolate, stearic acid, titanium dioxide

Questions or comments?

1-800-395-0689(Mon - Fri 9AM - 5PM EST)